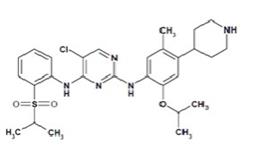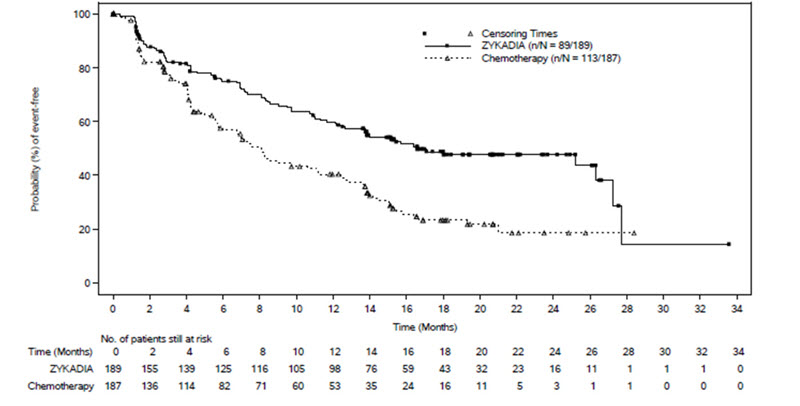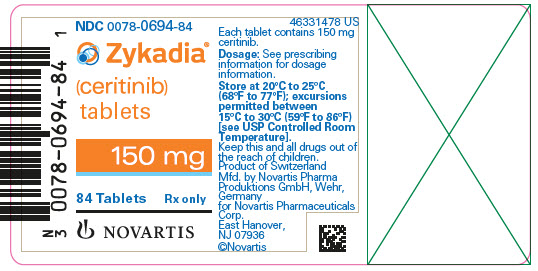 DRUG LABEL: ZYKADIA
NDC: 0078-0694 | Form: TABLET, FILM COATED
Manufacturer: Novartis Pharmaceuticals Corporation
Category: prescription | Type: HUMAN PRESCRIPTION DRUG LABEL
Date: 20251215

ACTIVE INGREDIENTS: CERITINIB 150 mg/1 1
INACTIVE INGREDIENTS: CELLULOSE, MICROCRYSTALLINE; HYDROXYPROPYL CELLULOSE; POVIDONE K30; CROSCARMELLOSE SODIUM; MAGNESIUM STEARATE; SILICON DIOXIDE; TALC; TITANIUM DIOXIDE; HYPROMELLOSE, UNSPECIFIED; POLYETHYLENE GLYCOL, UNSPECIFIED; FD&C BLUE NO. 2

HIGHLIGHTS OF PRESCRIBING INFORMATION

These highlights do not include all the information needed to use ZYKADIA safely and effectively. See full prescribing information for ZYKADIA.
ZYKADIA® (ceritinib) capsules, for oral use
ZYKADIA® (ceritinib) tablets, for oral use
Initial U.S. Approval: 2014

RECENT MAJOR CHANGES

Warnings and Precautions, Gastrointestinal Adverse Reactions (5.1) | 8/2021

1 INDICATIONS AND USAGE

ZYKADIA is a kinase inhibitor indicated for the treatment of adults with metastatic non-small cell lung cancer (NSCLC) whose tumors are anaplastic lymphoma kinase (ALK)-positive as detected by an FDA-approved test. (1, 2.1)

2 DOSAGE AND ADMINISTRATION

Recommended Dosage: 450 mg orally once daily with food. (2.2)

3 DOSAGE FORMS AND STRENGTHS

- Capsules: 150 mg (3)
- Tablets: 150 mg (3)

4 CONTRAINDICATIONS

None. (4)

5 WARNINGS AND PRECAUTIONS

- Gastrointestinal Adverse Reactions: ZYKADIA can cause gastrointestinal adverse reactions. If severe or intolerable, withhold if not responsive to antiemetics or antidiarrheals; upon improvement, resume ZYKADIA at a reduced dose. (2.3, 5.1)
- Hepatotoxicity: ZYKADIA can cause hepatotoxicity. Monitor liver laboratory tests at least monthly. Withhold then dose reduce, or permanently discontinue ZYKADIA. (2.3, 5.2)
- Interstitial Lung Disease/Pneumonitis: Occurred in 2.4% of patients. Permanently discontinue ZYKADIA in patients diagnosed with treatment-related interstitial lung disease (ILD)/pneumonitis. (2.3, 5.3)
- QT Interval Prolongation: ZYKADIA can cause QTc interval prolongation. Monitor electrocardiograms and electrolytes in patients with congestive heart failure, bradyarrhythmias, electrolyte abnormalities, or those who are taking medications that are known to prolong the QTc interval. Withhold then dose reduce, or permanently discontinue ZYKADIA. (2.3, 5.4)
- Hyperglycemia: ZYKADIA can cause hyperglycemia. Monitor fasting glucose prior to treatment and periodically thereafter. Initiate or optimize anti-hyperglycemic medications as indicated. Withhold, then dose reduce, or permanently discontinue ZYKADIA. (2.3, 5.5)
- Bradycardia: ZYKADIA can cause bradycardia. Monitor heart rate and blood pressure regularly. Withhold, then dose reduce, or permanently discontinue ZYKADIA. (2.3, 5.6)
- Pancreatitis: Elevations of lipase and/or amylase and pancreatitis can occur. Monitor lipase and amylase prior to treatment and periodically thereafter as clinically indicated. Withhold, then dose reduce ZYKADIA. (2.3, 5.7)
- Embryo-Fetal Toxicity: ZYKADIA can cause fetal harm. Advise females of reproductive potential of the potential risk to a fetus and to use effective contraception. (5.8, 8.1, 8.3)

6 ADVERSE REACTIONS

The most common adverse reactions (incidence of ≥ 25%) in patients treated with ZYKADIA 450 mg with food are diarrhea, nausea, abdominal pain, vomiting, and fatigue; and with ZYKADIA 750 mg under fasted conditions are diarrhea, nausea, vomiting, fatigue, abdominal pain, decreased appetite, and weight loss. (6)

To report SUSPECTED ADVERSE REACTIONS, contact Novartis Pharmaceuticals Corporation at 1-888-669-6682 or FDA at 1-800-FDA-1088 or www.fda.gov/medwatch.

7 DRUG INTERACTIONS

- CYP3A Inhibitors and Inducers: Avoid concurrent use of ZYKADIA with strong CYP3A inhibitors or inducers. If concurrent use of a strong CYP3A inhibitor is unavoidable, dose reduce ZYKADIA. (2.4, 7.1)
- CYP3A Substrates: Avoid coadministration of ZYKADIA with sensitive CYP3A substrates. (7.2)
- CYP2C9 Substrates: Avoid coadministration of ZYKADIA with CYP2C9 substrates for which minimal concentration changes may lead to serious toxicities. (7.2)

8 USE IN SPECIFIC POPULATIONS

- Lactation: Advise not to breastfeed. (8.2)
- Severe Hepatic Impairment: For patients with severe hepatic impairment (Child-Pugh C), dose reduce ZYKADIA. (8.6)

FULL PRESCRIBING INFORMATION

1 INDICATIONS AND USAGE

ZYKADIA® is indicated for the treatment of adult patients with metastatic non-small cell lung cancer (NSCLC) whose tumors are anaplastic lymphoma kinase (ALK)-positive as detected by an FDA-approved test [see Dosage and Administration (2.1)].

2 DOSAGE AND ADMINISTRATION

2.1 Patient Selection

Select patients for treatment of metastatic NSCLC with ZYKADIA based on the presence of ALK positivity in tumor specimens [see Clinical Studies (14.1)].

Information on FDA-approved tests for the detection of ALK rearrangements in NSCLC is available at: http://www.fda.gov/CompanionDiagnostics.

2.2 Recommended Dosage

The recommended dosage of ZYKADIA is 450 mg orally once daily with food until disease progression or unacceptable toxicity [see Clinical Pharmacology (12.3)].

If a dose of ZYKADIA is missed, make up that dose unless the next dose is due within 12 hours.

If vomiting occurs during the course of treatment, do not administer an additional dose and continue with the next scheduled dose of ZYKADIA.

2.3 Dosage Modifications for Adverse Reactions

Table 1: Recommended ZYKADIA Dose Reductions
Dose Reduction | Recommended Dosage
First-dose reduction | 300 mg taken orally once daily with food
Second-dose reduction | 150 mg taken orally once daily with food

Discontinue ZYKADIA for patients unable to tolerate 150 mg taken orally once daily with food.

Dosage modifications for selected adverse reactions of ZYKADIA are provided in Table 2. If dose reduction is required due to an adverse reaction not listed in Table 2, then reduce the daily dose of ZYKADIA by 150 mg.

Table 2: Recommended ZYKADIA Dosage Modifications for Adverse Reactions
Adverse Reaction | ZYKADIA Dose Modification
Gastrointestinal Adverse Reactions [see Warnings and Precautions (5.1)]
Severe or intolerable nausea, vomiting, or diarrhea despite optimal antiemetic or anti-diarrheal therapy | Withhold until improved, then resume ZYKADIA at the next lower dosage.
Hepatotoxicity [see Warnings and Precautions (5.2)]
ALT or AST elevation greater than 5 times ULN with total bilirubin elevation less than or equal to 2 times ULN | Withhold until recovery to baseline or less than or equal to 3 times ULN, then resume ZYKADIA at the next lower dosage.
ALT or AST elevation greater than 3 times ULN with total bilirubin elevation greater than 2 times ULN in the absence of cholestasis or hemolysis | Permanently discontinue ZYKADIA.
Interstitial Lung Disease/Pneumonitis [see Warnings and Precautions (5.3)]
Any Grade treatment-related ILD/pneumonitis | Permanently discontinue ZYKADIA.
QT Interval Prolongation [see Warnings and Precautions (5.4)]
QTc interval greater than 500 msec on at least 2 separate ECGs | Withhold until QTc interval is less than 481 msec or recovery to baseline if baseline QTc is greater than or equal to 481 msec, then resume ZYKADIA at the next lower dosage.
QTc interval prolongation in combination with torsades de pointes or polymorphic ventricular tachycardia or signs/symptoms of serious arrhythmia | Permanently discontinue ZYKADIA.
Hyperglycemia [see Warnings and Precautions (5.5)]
Persistent hyperglycemia greater than 250 mg/dL despite optimal anti-hyperglycemic therapy | Withhold until hyperglycemia is adequately controlled, then resume ZYKADIA at the next lower dosage. If adequate hyperglycemic control cannot be achieved with optimal medical management, discontinue ZYKADIA.
Bradycardia [see Warnings and Precautions (5.6)]
Symptomatic bradycardia that is not life-threatening | Withhold until recovery to asymptomatic bradycardia or to a heart rate of 60 bpm or above, evaluate concomitant medications known to cause bradycardia. If bradycardia cannot be attributed to another drug, resume ZYKADIA at the next lower dosage.
Clinically significant bradycardia requiring intervention or life-threatening bradycardia in patients taking a concomitant medication also known to cause bradycardia or a medication known to cause hypotension | Withhold until recovery to asymptomatic bradycardia or to a heart rate of 60 bpm or above. If the concomitant medication can be adjusted or discontinued, resume ZYKADIA at the next lower dosage with frequent monitoring.
Life-threatening bradycardia in patients who are not taking a concomitant medication also known to cause bradycardia or known to cause hypotension | Permanently discontinue ZYKADIA.
Pancreatitis [see Warnings and Precautions (5.7)]
Lipase or amylase elevation greater than 2 times ULN | Withhold until recovery to less than 1.5 times ULN, then resume ZYKADIA at the next lower dosage.
Abbreviations: AST, aspartate aminotransferase; ALT, alanine aminotransferase; ULN, upper limit of normal; ILD, interstitial lung disease; ECG, electrocardiogram; bpm, beats per minute.

2.4 Dosage Modification for Strong CYP3A Inhibitors

Avoid concurrent use of strong CYP3A inhibitors during treatment with ZYKADIA [see Drug Interactions (7.1), Clinical Pharmacology (12.3)].

If concurrent use of a strong CYP3A inhibitor is unavoidable, reduce the ZYKADIA dose by approximately one-third, rounded to the nearest multiple of the 150 mg dosage strength. After discontinuation of a strong CYP3A inhibitor, resume the ZYKADIA dose that was taken prior to initiating the strong CYP3A inhibitor.

2.5 Dosage Modification for Patients With Severe Hepatic Impairment

For patients with severe hepatic impairment (Child-Pugh C), reduce the ZYKADIA dose by approximately one-third, rounded to the nearest multiple of the 150 mg dosage strength [see Use in Specific Populations (8.6), Clinical Pharmacology (12.3)].

3 DOSAGE FORMS AND STRENGTHS

Capsules: 150 mg hard gelatin capsule with opaque blue cap and opaque white body containing a white to off-white powder. The opaque blue cap is marked in black ink with “LDK 150MG” and the opaque white body is marked in black ink with “NVR”.

Tablets: 150 mg film-coated tablet, light blue, round, biconvex with beveled edges, without score, debossed with “NVR” on one side and “ZY1” on the other side.

4 CONTRAINDICATIONS

None.

5 WARNINGS AND PRECAUTIONS

5.1 Gastrointestinal Adverse Reactions

Severe gastrointestinal adverse reactions occurred in patients treated with ZYKADIA 750 mg under fasted conditions [see Adverse Reactions (6.1)]. Diarrhea, nausea, vomiting, or abdominal pain occurred in 95% of 925 patients, including severe cases (Grade 3 or 4) in 14% of patients treated with ZYKADIA across clinical studies. Diarrhea, nausea, vomiting, or abdominal pain leading to dose interruptions or reductions occurred in 36% of patients and leading to treatment discontinuation occurred in 1.6% of patients.

The incidence and severity of gastrointestinal adverse reactions were reduced for patients treated with ZYKADIA 450 mg with food in a dose optimization study (ASCEND-8). Diarrhea, nausea, vomiting, or abdominal pain occurred in 79% of 108 patients treated with ZYKADIA at the recommended dose of 450 mg with food. Of these, 53% were Grade 1 events and 24% were Grade 2 events. One patient (0.9%) experienced Grade 3 diarrhea, and one patient (0.9%) experienced Grade 3 vomiting. One patient (0.9%) required dose adjustment due to vomiting. Eleven (10%) patients had diarrhea, nausea, vomiting, or abdominal pain that required at least one dose interruption.

Monitor and manage patients using standard of care, including antidiarrheals, antiemetics, or fluid replacement, as indicated. Withhold ZYKADIA if gastrointestinal adverse reaction is severe or intolerable and is not responsive to antiemetics or antidiarrheals. Upon improvement, resume ZYKADIA at a reduced dose [see Dosage and Administration (2.3)].

5.2 Hepatotoxicity

Drug-induced hepatotoxicity occurred in patients treated with ZYKADIA [see Adverse Reactions (6.1)]. Elevations in alanine aminotransferase (ALT) > 5 times the upper limit of normal (ULN) occurred in 28% and elevations in aspartate aminotransferase (AST) > 5 times ULN occurred in 16% of 925 patients across clinical studies. Concurrent elevations in ALT > 3 times the ULN and total bilirubin > 2 times the ULN, with alkaline phosphatase < 2 times the ULN occurred in 0.3% of patients across clinical studies. Approximately 1% of patients required permanent discontinuation due to hepatotoxicity.

Monitor with liver laboratory tests, including ALT, AST, and total bilirubin, once a month and as clinically indicated, with more frequent testing in patients who develop transaminase elevations. Based on the severity of the adverse reaction, withhold ZYKADIA with resumption at a reduced dose, or permanently discontinue ZYKADIA [see Dosage and Administration (2.3)].

5.3 Interstitial Lung Disease/Pneumonitis

Severe, life-threatening, or fatal interstitial lung diseases (ILD)/pneumonitis occurred in patients treated with ZYKADIA [see Adverse Reactions (6.1)]. Across clinical studies, ILD/pneumonitis was reported in 2.4% of 925 patients treated with ZYKADIA. Grade 3 or 4 ILD/pneumonitis was reported in 1.3% of patients, with fatal events reported in 0.2% of patients. Ten patients (1.1%) discontinued ZYKADIA across clinical studies due to ILD/pneumonitis.

Monitor patients for pulmonary symptoms indicative of ILD/pneumonitis. Exclude other potential causes of ILD/pneumonitis and permanently discontinue ZYKADIA in patients diagnosed with treatment-related ILD/pneumonitis [see Dosage and Administration (2.3)].

5.4 QT Interval Prolongation

QTc interval prolongation, which may lead to an increased risk for ventricular tachyarrhythmia (e.g., torsades de pointes) or sudden death, occurred in patients treated with ZYKADIA [see Adverse Reactions (6.1)]. Across clinical studies, 6% of 919 patients with at least one post-baseline electrocardiogram (ECG) assessment had an increase from baseline of QTc > 60 msec. Approximately 1.3% of patients taking ZYKADIA 750 mg under fasted conditions were found to have a QTc > 500 msec. ZYKADIA causes concentration-dependent increases in the QTc interval [see Clinical Pharmacology (12.2)]. Across clinical studies, 0.2% of patients discontinued ZYKADIA due to QTc prolongation.

When possible, avoid use of ZYKADIA in patients with congenital long QT syndrome. Conduct periodic monitoring with ECGs and electrolytes in patients with congestive heart failure, bradyarrhythmias, electrolyte abnormalities, or those who are taking medications that are known to prolong the QTc interval. Based on the severity of the adverse reaction, withhold ZYKADIA, with resumption at a reduced dose, or permanently discontinue ZYKADIA [see Dosage and Administration (2.3)].

5.5 Hyperglycemia

Hyperglycemia occurred in patients treated with ZYKADIA [see Adverse Reactions (6.1)]. Across clinical studies, Grade 3 or 4 hyperglycemia, based on laboratory values, occurred in 13% of 925 patients.

Monitor fasting serum glucose prior to the start of ZYKADIA treatment and periodically thereafter as clinically indicated. Initiate or optimize anti-hyperglycemic medications as indicated. Based on the severity of the adverse reaction, withhold ZYKADIA with resumption at a reduced dose, or permanently discontinue ZYKADIA [see Dosage and Administration (2.3)].

5.6 Bradycardia

Bradycardia occurred in patients treated with ZYKADIA [see Adverse Reactions (6.1)]. Across clinical studies, sinus bradycardia, defined as a heart rate < 50 beats per minute, was noted as a new finding in 1.1% of 925 patients. Bradycardia was reported as an adverse reaction in 1% of patients. No patient required discontinuation and 0.1% required interruption with subsequent dose reduction for bradycardia.

Avoid using ZYKADIA in combination with other products known to cause bradycardia (e.g., beta-blockers, non-dihydropyridine calcium channel blockers, clonidine, and digoxin) to the extent possible. Monitor heart rate and blood pressure regularly. Based on the severity of the adverse reaction, withhold ZYKADIA with resumption at a reduced dose upon resolution of bradycardia, or permanently discontinue ZYKADIA [see Dosage and Administration (2.3)].

5.7 Pancreatitis

Pancreatitis occurred in patients treated with ZYKADIA [see Adverse Reactions (6.1)]. Pancreatitis, including one fatality, occurred in less than 1% of patients receiving ZYKADIA in clinical studies. Grade 3 or 4 elevations of amylase occurred in 7% of patients receiving ZYKADIA across clinical studies, while Grade 3 or 4 elevations of lipase occurred in 14% of patients.

Monitor lipase and amylase prior to the start of ZYKADIA treatment and periodically thereafter as clinically indicated. Based on the severity of the laboratory abnormalities, withhold ZYKADIA with resumption at a reduced dose [see Dosage and Administration (2.3)].

5.8 Embryo-Fetal Toxicity

Based on its mechanism of action and findings from animal studies, ZYKADIA can cause fetal harm when administered to a pregnant woman. In animal studies, administration of ceritinib to rats and rabbits during organogenesis at maternal plasma exposures below the recommended human dose caused increases in skeletal anomalies in rats and rabbits.

Advise pregnant women of the potential risk to a fetus. Advise females of reproductive potential to use effective contraception during treatment with ZYKADIA and for 6 months following completion of therapy. Based on the potential for genotoxicity, advise males with female partners of reproductive potential to use condoms during treatment with ZYKADIA and for 3 months following completion of therapy [see Use in Specific Populations (8.1, 8.3), Nonclinical Toxicology (13.1)].

6 ADVERSE REACTIONS

The following clinically significant adverse reactions are described elsewhere in the labeling:

- Gastrointestinal Adverse Reactions [see Warnings and Precautions (5.1)]
- Hepatotoxicity [see Warnings and Precautions (5.2)]
- Interstitial Lung Disease/Pneumonitis [see Warnings and Precautions (5.3)]
- QT Interval Prolongation [see Warnings and Precautions (5.4)]
- Hyperglycemia [see Warnings and Precautions (5.5)]
- Bradycardia [see Warnings and Precautions (5.6)]
- Pancreatitis [see Warnings and Precautions (5.7)]

6.1 Clinical Trials Experience

Because clinical trials are conducted under widely varying conditions, adverse reaction rates observed in the clinical trials of a drug cannot be directly compared to rates in the clinical trials of another drug and may not reflect the rates observed in practice.

The data in the Warnings and Precautions section reflect exposure to ZYKADIA 750 mg once daily under fasted conditions in 925 patients with ALK-positive NSCLC across seven clinical studies, including ASCEND-4 and ASCEND-1, described below, a randomized active-controlled study, two single arm studies, and two dose-escalation studies. The majority of patients enrolled in these studies had received prior treatment with chemotherapy and/or crizotinib for NSCLC. Among these 925 patients, the most common adverse reactions (≥ 25% incidence) were diarrhea, nausea, vomiting, fatigue, abdominal pain, decreased appetite, and weight loss. Approximately 45% of patients initiating treatment with ZYKADIA 750 mg under fasted conditions had an adverse reaction that required at least one dose reduction and 66% of patients had an adverse reaction that required at least one dose interruption. The median time to first dose reduction due to any reason was 7 weeks.

Dose Optimization Study: Dosing Regimen of 450 mg Daily With Food

In ASCEND-8, a dose optimization study, ZYKADIA 450 mg daily with food (N = 108) was compared to 750 mg daily under fasted conditions (N = 110) in both previously treated and untreated patients with ALK-positive NSCLC. The overall safety profile of ZYKADIA 450 mg with food was consistent with ZYKADIA 750 mg fasted, except for a reduction in gastrointestinal adverse reactions, while achieving comparable steady-state exposure [see Clinical Pharmacology (12.3)]. The most common adverse reactions (≥ 25% incidence) in the 450 mg with food arm were diarrhea, nausea, abdominal pain, vomiting, and fatigue. The incidence and severity of gastrointestinal adverse reactions (diarrhea 59%, nausea 43%, and vomiting 38%) were reduced for patients treated with ZYKADIA 450 mg with food; Grade ≥ 3 adverse reactions were reported in two patients (1.9%): Grade 3 diarrhea and Grade 3 vomiting in one patient each [see Warnings and Precautions (5.1)].

In patients treated with ZYKADIA 450 mg with food, 24% of patients had an adverse reaction that required at least one dose reduction and 56% of patients had an adverse reaction that required at least one dose interruption. The median time to first dose reduction due to any reason was 8 weeks.

Previously Untreated ALK-Positive Metastatic NSCLC

The safety of ZYKADIA was evaluated in ASCEND-4, an open-label, randomized, active-controlled multicenter study of 376 previously untreated ALK-positive NSCLC patients [see Clinical Studies (14.1)]. Patients received ZYKADIA 750 mg daily (N = 189) under fasted conditions or chemotherapy and maintenance chemotherapy (N = 187). Chemotherapy regimens were pemetrexed (500 mg/m^2) and investigator’s choice of cisplatin (75 mg/m^2) or carboplatin [area under the curve (AUC) of 5 - 6 mg*min/mL] administered every 21 days. Patients who completed 4 cycles of chemotherapy without progressive disease received pemetrexed (500 mg/m^2) as single-agent maintenance therapy every 21 days. The median duration of exposure to ZYKADIA was 18 months.

The demographic characteristics of the study population were 57% female, median age 54 years (range, 22 to 81 years), 22% age 65 years or older, 54% white, 42% Asian, 2% black, and 2% other races. Patients were enrolled in Europe (53%), Asia Pacific (42%), and South America (5%) regions. The majority of patients had adenocarcinoma (97%), never smoked (61%), and 32% had brain metastases at screening.

The following fatal adverse reactions occurred in 4 patients treated with ZYKADIA: Myocardial infarction, respiratory tract infection, pneumonitis, and unknown cause.

Serious adverse reactions were reported in 38% of patients treated with ZYKADIA. The most frequent serious adverse reactions were pneumonia (4%), pleural effusion (4%), vomiting (4%), nausea (3%), dyspnea (3%), hyperglycemia (3%), AST increased (2%), lung infection (2%), and pericardial effusion (2%).

Among patients treated with ZYKADIA, dose interruptions due to adverse reactions occurred in 77%, dose reductions were required in 66%, and adverse reactions that led to discontinuation of therapy occurred in 12% of patients. The most frequent adverse reactions, reported in at least 10% of patients treated with ZYKADIA, that led to dose interruptions or reductions were: Increased ALT (48%), increased AST (34%), vomiting (15%), increased blood creatinine (14%), increased gamma-glutamyl transpeptidase (GGT) (13%), diarrhea (13%), and nausea (13%). The most frequent adverse reactions that led to discontinuation of ZYKADIA in 1% or more of patients in ASCEND-4 were increased blood creatinine (2.1%), increased amylase (1.1%), and increased lipase (1.1%).

Tables 3 and 4 summarize adverse reactions and laboratory abnormalities, respectively, in ASCEND-4.

Table 3: Adverse Reactions (> 10% for All Grades* or ≥ 2% for Grades 3-4) of Patients in ASCEND-4
 | ZYKADIA N = 189 |  | Chemotherapy N = 175 a
 | All Grades | Grade 3-4 | All Grades | Grade 3-4
 | % | % | % | %
Gastrointestinal**
Diarrhea | 85 | 4.8 | 11 | 1.1
Nausea | 69 | 2.6 | 55 | 5
Vomiting | 67 | 5 | 36 | 6
Abdominal painb | 40 | 3.7 | 13 | 0
Constipation | 20 | 0 | 22 | 0
Esophageal disorderc | 15 | 0.5 | 8 | 0.6
General
Fatigued | 45 | 7 | 49 | 6
Non-cardiac chest pain | 21 | 1.1 | 10 | 0.6
Back pain | 19 | 1.6 | 18 | 2.3
Pyrexia | 19 | 0 | 14 | 1.1
Pain in extremity | 13 | 0 | 7 | 0
Musculoskeletal pain | 11 | 0.5 | 6 | 0.6
Pruritus | 11 | 0.5 | 5 | 0
Metabolism and Nutrition
Decreased appetite | 34 | 1.1 | 32 | 1.1
Weight loss | 24 | 3.7 | 15 | 0.6
Respiratory
Cough | 25 | 0 | 17 | 0
Skin
Rashe | 21 | 1.1 | 8 | 0.6
Neurologic
Headache | 19 | 0.5 | 13 | 1.1
Dizziness | 12 | 1.1 | 10 | 0.6
Cardiac
Prolonged QT interval | 12 | 2.6 | 1.1 | 0.6
Pericarditisf | 4.2 | 1.6 | 2.3 | 1.1
*National Cancer Institute Common Terminology Criteria for Adverse Events (version 4.03).
**For frequency of gastrointestinal adverse reactions at the recommended dose of 450 mg with food [see Warnings and Precautions (5.1), Adverse Reactions (6.1)].
aTwelve patients randomized to chemotherapy did not receive study drug.
bAbdominal pain (abdominal pain, abdominal pain upper, abdominal discomfort, and epigastric discomfort).
cEsophageal disorder (dyspepsia, gastroesophageal reflux disease, and dysphagia).
dFatigue (fatigue and asthenia).
eRash (rash, dermatitis acneiform, rash maculo-papular).
fPericarditis (pericardial effusion and pericarditis).

Additional clinically significant adverse reactions occurring in 2% or more of patients treated with ZYKADIA 750 mg under fasted conditions included: vision disorder (4% comprised of vision impairment, blurred vision, photopsia, accommodation disorder, presbyopia, reduced visual acuity, or vitreous floaters), bradycardia (4%), ILD/pneumonitis (2%), hepatotoxicity (2%), and renal failure (2%). In addition, the adverse reaction of photosensitivity was reported in 1.1% of patients.

Table 4: Laboratory Abnormalities Occurring in > 10% (All Grades*) of Patients in ASCEND-4
 | ZYKADIA N = 189 |  | Chemotherapy N = 175 a
 | All Grades | Grade 3-4 | All Grades | Grade 3-4
 | % | % | % | %
Chemistry
Increased ALT | 91 | 34 | 65 | 3.4
Increased AST | 86 | 21 | 58 | 2.3
Increased GGT | 84 | 49 | 67 | 10
Increased alkaline phosphatase | 81 | 12 | 47 | 1.7
Increased creatinine | 77 | 4.2 | 37 | 0.6
Hyperglycemia | 53 | 10 | 67 | 10
Hypophosphatemia | 38 | 3.7 | 27 | 4.0
Increased amylase | 37 | 8 | 43 | 4.5
Hyperbilirubinemia (total) | 15 | 0.5 | 6 | 0.6
Increased lipaseb | 13 | 6 | 7 | 0.6
Hematology
Anemia | 67 | 4.2 | 84 | 11
Neutropenia | 27 | 2.1 | 58 | 20
Thrombocytopenia | 16 | 1.0 | 38 | 4.6
Abbreviations: ALT, alanine aminotransferase; AST, aspartate aminotransferase; GGT, gamma-glutamyl transpeptidase.
*National Cancer Institute Common Terminology Criteria for Adverse Events (version 4.03).
aTwelve patients randomized to chemotherapy did not receive study drug.
bIn the ZYKADIA arm, no patients had baseline lipase laboratory assessments, 112 had post-baseline assessments. In the chemotherapy arm, one patient had baseline lipase laboratory assessments but no post-baseline assessment; 49 patients had post-baseline assessments.

Previously Treated ALK-Positive Metastatic NSCLC

The safety of ZYKADIA was evaluated in ASCEND-1, a multicenter, single-arm, open-label clinical study of 255 ALK-positive patients (246 patients with NSCLC and 9 patients with other cancers who received ZYKADIA at a dose of 750 mg daily under fasted conditions) [see Clinical Studies (14.2)]. The median duration of exposure to ZYKADIA was 6 months.

The study population characteristics were: Median age 53 years, age less than 65 (84%), female (53%), white (63%), Asian (34%), NSCLC adenocarcinoma histology (90%), never or former smoker (97%), Eastern Cooperative Oncology Group Performance Status (ECOG PS) 0 or 1 (89%), brain metastases (49%), and number of prior therapies 2 or more (67%).

Fatal adverse reactions in patients treated with ZYKADIA occurred in 5% of patients, consisting of: Pneumonia (4 patients), respiratory failure, ILD/pneumonitis, pneumothorax, gastric hemorrhage, general physical health deterioration, pulmonary tuberculosis, cardiac tamponade, and sepsis (1 patient each).

Serious adverse reactions reported in 2% or more of patients in ASCEND-1 were convulsion, pneumonia, ILD/pneumonitis, dyspnea, dehydration, hyperglycemia, and nausea.

Dose reductions due to adverse reactions occurred in 59% of patients treated with ZYKADIA. The most frequent adverse reactions, reported in at least 10% of patients, that led to dose reductions or interruptions were: Increased ALT (29%), nausea (20%), increased AST (16%), diarrhea (16%), and vomiting (16%). Discontinuation of therapy due to adverse reactions occurred in 10% of patients treated with ZYKADIA. The most frequent adverse reactions that led to discontinuation in 1% or more of patients in ASCEND-1 were pneumonia, ILD/pneumonitis, and decreased appetite.

Tables 5 and 6 summarize adverse reactions and laboratory abnormalities, respectively, in ASCEND-1.

Table 5: Adverse Reactions (> 10% for All Grades* or ≥ 2% for Grades 3-4) in ALK-Positive Patients Treated With ZYKADIA in ASCEND-1
 | ZYKADIA N = 255
 | All Grades | Grade 3-4
 | % | %
Gastrointestinal**
Diarrhea | 86 | 6
Nausea | 80 | 4
Vomiting | 60 | 4
Abdominal paina | 54 | 2
Constipation | 29 | 0
Esophageal disorderb | 16 | 1
General
Fatiguec | 52 | 5
Metabolism and Nutrition
Decreased appetite | 34 | 1
Skin
Rashd | 16 | 0
Respiratory
Interstitial lung disease/pneumonitis | 4 | 3
Abbreviation: ALK, anaplastic lymphoma kinase.
*National Cancer Institute Common Terminology Criteria for Adverse Events (version 4.03).
**For frequency of gastrointestinal adverse reactions at the recommended dose of 450 mg with food [see Warnings and Precautions (5.1), Adverse Reactions (6.1)].
aAbdominal pain (abdominal pain, upper abdominal pain, abdominal discomfort, and epigastric discomfort).
bEsophageal disorder (dyspepsia, gastroesophageal reflux disease, and dysphagia).
cFatigue (fatigue and asthenia).
dRash (rash, maculopapular rash, and acneiform dermatitis).

Additional clinically significant adverse reactions occurring in 2% or more of patients treated with ZYKADIA 750 mg under fasted conditions included neuropathy (17% comprised of paresthesia, muscular weakness, gait disturbance, peripheral neuropathy, hypoesthesia, peripheral sensory neuropathy, dysesthesia, neuralgia, peripheral motor neuropathy, hypotonia, or polyneuropathy), vision disorder (9% comprised of vision impairment, blurred vision, photopsia, accommodation disorder, presbyopia, or reduced visual acuity), prolonged QT interval (4%), and bradycardia (3%). In addition, the adverse reaction of photosensitivity was reported in 1.2% of patients.

Table 6: Key Laboratory Abnormalities Occurring in > 10% (All Grades*) of ALK-Positive Patients Treated With ZYKADIA in ASCEND-1
 | ZYKADIA N = 255
 | All Grades | Grade 3-4
 | % | %
Hematology
Anemia | 84 | 5
Chemistry
Increased ALT | 80 | 27
Increased AST | 75 | 13
Increased creatinine | 58 | 2
Hyperglycemia | 49 | 13
Hypophosphatemia | 36 | 7
Increased lipase | 28 | 10
Hyperbilirubinemia (total) | 15 | 1
Abbreviations: ALT, alanine aminotransferase; AST, aspartate aminotransferase; ALK, anaplastic lymphoma kinase.
*National Cancer Institute Common Terminology Criteria for Adverse Events (version 4.03).

7 DRUG INTERACTIONS

7.1 Effect of Other Drugs on ZYKADIA

Strong CYP3A Inhibitors

A strong CYP3A4/P-gp inhibitor (ketoconazole) increased the systemic exposure of ceritinib [see Clinical Pharmacology (12.3)], which may increase the incidence and severity of adverse reactions of ZYKADIA. Avoid concurrent use of strong CYP3A inhibitors during treatment with ZYKADIA. If concurrent use of strong CYP3A inhibitors is unavoidable, reduce the ZYKADIA dose [see Dosage and Administration (2.4)].

Do not consume grapefruit and grapefruit juice as they may inhibit CYP3A.

Strong CYP3A Inducers

A strong CYP3A4/P-gp inducer (rifampin) decreased the systemic exposure of ceritinib [see Clinical Pharmacology (12.3)], which may decrease the efficacy of ZYKADIA. Avoid concurrent use of strong CYP3A inducers during treatment with ZYKADIA.

7.2 Effect of ZYKADIA on Other Drugs

CYP3A Substrates

Ceritinib increased the systemic exposure of a sensitive CYP3A substrate (midazolam) [see Clinical Pharmacology (12.3)]. Avoid coadministration of ZYKADIA with sensitive CYP3A substrates. If concomitant use is unavoidable, consider dose reduction of the sensitive CYP3A substrate(s). If ZYKADIA is coadministered with other CYP3A substrates, refer to the CYP3A substrate labeling for dosage recommendation with strong CYP3A inhibitors.

CYP2C9 Substrates

Ceritinib increased the systemic exposure of a CYP2C9 substrate (warfarin) [see Clinical Pharmacology (12.3)]. Increase the frequency of INR monitoring if coadministration with warfarin is unavoidable as the anti-coagulant effect of warfarin may be enhanced.

Avoid coadministration of ZYKADIA with CYP2C9 substrates for which minimal concentration changes may lead to serious toxicities. If concomitant use of such CYP2C9 substrates is unavoidable, consider dose reduction for the coadministered CYP2C9 substrates.

7.3 Drugs That Prolong QT Interval

ZYKADIA causes concentration-dependent increases in the QTc interval. When possible, avoid coadministration of ZYKADIA with other products with a known potential to prolong the QTc interval [see Warnings and Precautions (5.4), Clinical Pharmacology (12.2)].

7.4 Drugs That Cause Bradycardia

ZYKADIA can cause bradycardia. When possible, avoid coadministration of ZYKADIA with other products known to cause bradycardia [see Warnings and Precautions (5.6), Clinical Pharmacology (12.2)].

8 USE IN SPECIFIC POPULATIONS

8.1 Pregnancy

Risk Summary

Based on animal studies and its mechanism of action [see Clinical Pharmacology (12.1)], ZYKADIA can cause fetal harm when administered to a pregnant woman. The limited available data on the use of ZYKADIA in pregnant women are insufficient to inform a risk. Administration of ceritinib to rats and rabbits during the period of organogenesis at maternal plasma exposures below the recommended human dose caused increases in skeletal anomalies in rats and rabbits (see Data). Advise a pregnant woman of the potential risk to a fetus.

In the U.S. general population, the estimated background risk of major birth defects and miscarriage in clinically recognized pregnancies are 2% to 4% and 15% to 20%, respectively.

Data

Animal Data

In an embryo-fetal development study in which pregnant rats were administered daily doses of ceritinib during organogenesis, dose-related skeletal anomalies were observed at doses as low as 50 mg/kg (less than 0.5-fold the human exposure by AUC at the recommended dose). Findings included delayed ossifications and skeletal variations.

In pregnant rabbits administered ceritinib daily during organogenesis, dose-related skeletal anomalies, including incomplete ossification, were observed at doses equal to or > 2 mg/kg/day (approximately 0.015-fold the human exposure by AUC at the recommended dose). A low incidence of visceral anomalies, including absent or malpositioned gallbladder and retroesophageal subclavian cardiac artery, was observed at doses equal to or > 10 mg/kg/day (approximately 0.13-fold the human exposure by AUC at the recommended dose). Maternal toxicity and abortion occurred in rabbits at doses of 35 mg/kg or greater. In addition, embryolethality was observed in rabbits at a dose of 50 mg/kg.

8.2 Lactation

Risk Summary

There are no data regarding the presence of ceritinib or its metabolites in human milk, the effects of ceritinib on the breastfed child or its effects on milk production. Because of the potential for serious adverse reactions in breastfed children, advise women not to breastfeed during treatment with ZYKADIA and for 2 weeks following completion of therapy.

8.3 Females and Males of Reproductive Potential

Pregnancy Testing

Verify pregnancy status in females of reproductive potential prior to initiating ZYKADIA [see Use in Specific Populations (8.1)].

Contraception

ZYKADIA can cause fetal harm when administered to a pregnant woman [see Use in Specific Populations (8.1)].

Females

Advise females of reproductive potential to use effective contraception during treatment with ZYKADIA and for 6 months following completion of therapy.

Males

Based on the potential for genotoxicity, advise males with female partners of reproductive potential to use condoms during treatment with ZYKADIA and for 3 months following completion of therapy [see Nonclinical Toxicology (13.1)].

8.4 Pediatric Use

The safety and effectiveness of ZYKADIA in pediatric patients have not been established.

8.5 Geriatric Use

Of the 925 patients in clinical studies of ZYKADIA, 18% were 65 years or older, while 5% were 75 years or older. No overall differences in safety or effectiveness were observed between these subjects and younger subjects.

8.6 Hepatic Impairment

For patients with severe hepatic impairment (Child-Pugh C), reduce the dose of ZYKADIA [see Dosage and Administration (2.5)]. No dose adjustment is recommended for patients with mild (Child-Pugh A) or moderate (Child-Pugh B) hepatic impairment.

11 DESCRIPTION

Ceritinib is a kinase inhibitor for oral administration. The molecular formula for ceritinib is C28H36N5O3ClS. The molecular weight is 558.14 g/mol. Ceritinib is described chemically as 5-Chloro-N4-[2-[(1-methylethyl)sulfonyl]phenyl]-N2-[5-methyl-2-(1-methylethoxy)-4-(4-piperidinyl)phenyl]-2,4-pyrimidinediamine.

The chemical structure of ceritinib is shown below:

Ceritinib is a white to almost white or light yellow powder.

ZYKADIA is supplied as printed hard-gelatin capsules containing 150 mg of ceritinib and the following inactive ingredients: colloidal silicon dioxide, hard gelatin capsule shells, low substituted hydroxypropyl cellulose, magnesium stearate, microcrystalline cellulose, and sodium starch glycolate. The capsule shell is composed of FD&C Blue # 2, gelatin, and titanium dioxide.

ZYKADIA is supplied as film-coated tablets containing 150 mg of ceritinib and the following inactive ingredients: colloidal silicon dioxide, croscarmellose sodium, low-substituted hydroxypropyl cellulose, magnesium stearate, microcrystalline cellulose and povidone. The tablet coating contains FD&C Blue # 2 aluminum lake, hypromellose, polyethylene glycol 4000, talc, and titanium dioxide.

12 CLINICAL PHARMACOLOGY

12.1 Mechanism of Action

Ceritinib is a kinase inhibitor. Targets of ceritinib inhibition identified in either biochemical or cellular assays at clinically relevant concentrations include ALK, insulin-like growth factor 1 receptor (IGF-1R), insulin receptor (InsR), and ROS1. Among these, ceritinib is most active against ALK. Ceritinib inhibited autophosphorylation of ALK, ALK-mediated phosphorylation of the downstream signaling protein STAT3, and proliferation of ALK-dependent cancer cells in in vitro and in vivo assays.

Ceritinib inhibited the in vitro proliferation of cell lines expressing EML4-ALK and NPM-ALK fusion proteins and demonstrated dose-dependent inhibition of EML4-ALK-positive NSCLC xenograft growth in mice and rats. Ceritinib exhibited dose-dependent anti-tumor activity in mice bearing EML4-ALK-positive NSCLC xenografts with demonstrated resistance to crizotinib, at concentrations within a clinically relevant range.

12.2 Pharmacodynamics

Cardiac Electrophysiology

Twelve of 919 patients (1.3%) treated with ZYKADIA 750 mg once daily under fasted conditions with at least one post-baseline ECG assessment were found to have a QTc > 500 msec and 58 patients (6%) had an increase from baseline QTc > 60 msec. In ASCEND-4, a central tendency analysis of the QTc data at average steady-state concentrations demonstrated that the upper bound of the 2-sided 90% CI for QTc was 15.3 msec at ZYKADIA 750 mg once daily under fasted conditions. A pharmacokinetic/pharmacodynamic analysis suggested concentration-dependent QTc interval prolongation [see Warnings and Precautions (5.4)].

Ten of 925 patients (1.1%) had bradycardia defined as < 50 beats per minute [see Warnings and Precautions (5.6)].

12.3 Pharmacokinetics

After a single oral administration of ZYKADIA in patients, AUC and Cmax increased dose proportionally over 50 mg to 750 mg under fasted conditions.

Following ZYKADIA 750 mg once daily under fasted conditions, steady state was reached by 15 days with a geometric mean accumulation ratio of 6.2 after 3 weeks. Systemic exposure increased in a greater than dose proportional manner after repeat doses of 50 mg to 750 mg once daily under fasted conditions.

Absorption

After a single oral administration of ZYKADIA in patients, peak plasma levels (Cmax) of ceritinib were achieved around 4 to 6 hours.

Food Effect

A food effect study conducted in healthy subjects with a single 500 mg dose of ZYKADIA capsules showed that a high-fat meal (containing approximately 1000 calories and 58 grams of fat) increased ceritinib AUC by 73% and Cmax by 41% and a low-fat meal (containing approximately 330 calories and 9 grams of fat) increased ceritinib AUC by 58% and Cmax by 43% as compared with the fasted conditions.

A food effect study conducted in healthy subjects with a single 750 mg dose of ZYKADIA tablets showed that a high-fat meal (containing approximately 1000 calories and 58 grams of fat) increased ceritinib AUC by 64% and Cmax by 58% and a low-fat meal (containing approximately 330 calories and 9 grams of fat) increased ceritinib AUC by 39% and Cmax by 42% as compared with the fasted conditions.

Dose Optimization Study: Dosing Regimen of 450 mg Daily With Food

In a dose optimization study (ASCEND-8) in patients receiving 450 mg dose of ZYKADIA capsules daily with food (approximately 100 to 500 calories and 1.5 to 15 grams of fat) or 750 mg daily under fasted conditions, there was no clinically meaningful difference in the systemic steady-state exposure of ceritinib (AUC) between the 450 mg with food arm and the 750 mg fasted arm.

Distribution

Ceritinib is 97% bound to human plasma proteins, independent of drug concentration. The geometric mean apparent volume of distribution (Vd/F) is 4230 L following a single 750 mg ZYKADIA dose under fasted conditions in patients. Ceritinib also has a slight preferential distribution to red blood cells, relative to plasma, with a mean in vitro blood-to-plasma ratio of 1.35.

Elimination

Following a single 750 mg ZYKADIA dose under fasted conditions, the geometric mean apparent plasma terminal half-life (t1/2) of ceritinib was 41 hours in patients. Ceritinib demonstrates nonlinear PK over time. The geometric mean apparent clearance (CL/F) of ceritinib was lower at steady state (33.2 L/h) after 750 mg daily dosing than after a single 750 mg dose (88.5 L/h).

Metabolism: In vitro studies demonstrated that CYP3A was the major enzyme involved in the metabolic clearance of ceritinib. Following oral administration of a single 750 mg radiolabeled dose under fasted conditions, ceritinib was the main circulating component (82%) in human plasma.

Excretion: Following oral administration of a single 750 mg radiolabeled dose under fasted conditions, 92% of the administered dose was recovered in the feces (with 68% as unchanged parent compound) while 1.3% of the administered dose was recovered in the urine.

Specific Populations

Age, sex, race, body weight, and mild-to-moderate renal impairment (CLcr 30 to < 90 mL/min estimated with Cockcroft-Gault) has no clinically important effect on the systemic exposure of ceritinib based on population pharmacokinetic analyses. Patients with severe renal impairment (CLcr < 30 mL/min) were not included in the clinical trial.

Patients with Hepatic Impairment: Following a single 750 mg ZYKADIA dose under fasted conditions, the geometric mean systemic exposure (AUC0-INF) of ceritinib was increased by 66% and unbound ceritinib AUC0-INF was increased by 108% in subjects with severe (Child-Pugh C) hepatic impairment compared to subjects with normal hepatic function [see Dosage and Administration (2.5)]. Total and unbound systemic exposure of ceritinib were similar in subjects with mild (Child-Pugh A) to moderate (Child-Pugh B) hepatic impairment compared to subjects with normal hepatic function.

Drug Interaction Studies

Effect of Strong CYP3A/P-gp Inhibitors on Ceritinib: Coadministration of a single 450 mg ZYKADIA dose under fasted conditions with ketoconazole (a strong CYP3A/P-gp inhibitor) for 14 days increased ceritinib AUC by 2.9-fold and Cmax by 22%. The steady-state AUC of ceritinib at a dose of 450 mg once daily under fasted conditions with ketoconazole for 14 days was predicted to be similar to the steady-state AUC of ceritinib at a dose of 750 mg alone under fasted conditions.

Effect of Strong CYP3A/P-gp Inducers on Ceritinib: Coadministration of a single 750 mg ZYKADIA dose under fasted conditions with rifampin (a strong CYP3A/P-gp inducer) for 14 days decreased ceritinib AUC by 70% and Cmax by 44%.

Effect of Ceritinib on CYP3A Substrates: Coadministration of a single dose of midazolam (a sensitive CYP3A substrate) following 3 weeks of ZYKADIA (750 mg daily under fasted conditions) increased the midazolam AUC by 5.4-fold and Cmax by 1.8-fold compared to midazolam administered alone [see Drug Interactions (7.2)].

Effect of Ceritinib on CYP2C9 Substrates: Coadministration of a single dose of warfarin (a CYP2C9 substrate) following 3 weeks of ZYKADIA (750 mg daily under fasted conditions) increased the S-warfarin AUC by 54% with no change in Cmax compared to warfarin administered alone [see Drug Interactions (7.2)].

Effect of Acid Reducing Agents on Ceritinib: Coadministration of a single 750 mg ZYKADIA dose under fasted conditions with a proton pump inhibitor (esomeprazole) for 6 days in healthy subjects decreased ceritinib AUC by 76% and Cmax by 79%; however, coadministration of a single 750 mg ZYKADIA dose under fasted conditions with proton pump inhibitors for 6 days in a subgroup of patients from ASCEND-1 suggested less effect on ceritinib exposure than that observed in healthy subjects as AUC decreased by 30% and Cmax decreased by 25% and no clinically meaningful effect on ceritinib exposure was observed at steady-state.

Effect of Transporters on Ceritinib Disposition: Ceritinib is a substrate of efflux transporter P-gp, but is not a substrate of BCRP, MRP2, OCT1, OAT2, or OATP1B1 in vitro.

Effect of Ceritinib on Transporters: Based on in vitro data, ceritinib is unlikely to inhibit P-gp, BCRP, MRP2, OATP1B1, OATP1B3, OAT1, OAT3, OCT1, or OCT2 at clinical concentrations.

13 NONCLINICAL TOXICOLOGY

13.1 Carcinogenesis, Mutagenesis, Impairment of Fertility

Carcinogenicity studies have not been performed with ceritinib.

Ceritinib was not mutagenic in vitro in the bacterial reverse mutation (Ames) assay but induced numerical aberrations (aneugenic) in the in vitro cytogenetic assay using human lymphocytes, and micronuclei in the in vitro micronucleus test using TK6 cells. Ceritinib was not clastogenic in the in vivo rat micronucleus assay.

There are no data on the effect of ceritinib on human fertility. Fertility/early embryonic development studies were not conducted with ceritinib. There were no adverse effects on male or female reproductive organs in general toxicology studies conducted in monkeys and rats at exposures ≥ 0.5- and 1.5-fold, respectively, of the human exposure by AUC at the recommended dose.

13.2 Animal Toxicology and/or Pharmacology

Target organs in nonclinical animal models included, but were not limited to, the pancreas, biliopancreatic/bile ducts, gastrointestinal tract, and liver. Pancreatic focal acinar cell atrophy was observed in rats at 1.5-fold the human exposure by AUC at the recommended dose. Biliopancreatic duct and bile duct necrosis was observed in rats at exposures ≥ 5% of the human exposure by AUC at the recommended dose. Bile duct inflammation and vacuolation were also noted in monkeys at exposures ≥ 0.5-fold the human exposure by AUC at the recommended dose. Frequent minimal necrosis and hemorrhage of the duodenum was exhibited in monkeys at 0.5-fold the human exposure by AUC, and in rats at an exposure similar to that observed clinically.

Ceritinib crossed the blood brain barrier in rats with a brain-to-blood exposure (AUCinf) ratio of approximately 15%.

14 CLINICAL STUDIES

14.1 Previously Untreated ALK-Positive Metastatic NSCLC

The efficacy of ZYKADIA for the treatment of patients with ALK-positive NSCLC who had not received prior systemic therapy for metastatic disease was evaluated in an open-label, randomized, active-controlled, multicenter study (ASCEND-4, NCT01828099). Patients were required to have World Health Organization (WHO) performance status 0-2 and ALK-positive NSCLC as identified by the VENTANA ALK (D5F3) CDx Assay. Neurologically stable patients with central nervous system (CNS) metastases that did not require increasing doses of steroids to manage CNS symptoms were permitted to enroll. Patients with uncontrolled diabetes mellitus; a history of ILD or interstitial pneumonitis; or a history of pancreatitis, or increased amylase, or lipase that was due to pancreatic disease were not eligible.

The major efficacy outcome measure was progression-free survival (PFS) as determined by Blinded Independent Review Committee (BIRC) according to RECIST v1.1. Additional efficacy outcome measures were overall survival (OS), overall response rate (ORR) and duration of response (DOR) determined by BIRC, overall intracranial response rate (OIRR), duration of intracranial response (DOIR) determined by BIRC neuro-radiologist, and patient reported outcomes.

Patients were randomized 1:1 to receive ZYKADIA 750 mg orally daily under fasted conditions or chemotherapy and maintenance chemotherapy. Randomization was stratified by WHO performance status, prior adjuvant/neoadjuvant chemotherapy and presence or absence of brain metastases. Patients randomized to chemotherapy received pemetrexed (500 mg/m^2) and investigator’s choice of cisplatin (75 mg/m^2) or carboplatin (AUC of 5 - 6 mg*min/mL) administered on Day 1 of each 21-day cycle for a maximum of 4 cycles followed by pemetrexed (500 mg/m^2) every 21 days. Treatment in both arms was continued until disease progression or unacceptable toxicity.

The study population characteristics were: 57% female, median age 54 years (range, 22 to 81 years), 22% age 65 years or older, 54% white, 42% Asian, 2% black, and 2% other races. The majority of patients had adenocarcinoma (97%) and never smoked (61%). CNS metastases were present in 32% (n = 121) of patients. Approximately half (n = 55) had measurable CNS metastases as determined by BIRC neuro-radiologist and 71% (n = 39) of these patients received no prior intracranial radiotherapy. Of those randomized to chemotherapy, 43% received ZYKADIA as the next antineoplastic therapy after platinum-based chemotherapy.

Efficacy results from ASCEND-4 are summarized in Table 7 and Figure 1.

Table 7: Efficacy Results by BIRC Assessment in ASCEND-4
Efficacy Parameter | ZYKADIA (N = 189) | Chemotherapy (N = 187)
Progression-Free Survival
Number of events, n (%) | 89 (47%) | 113 (60%)
Progressive disease, n (%) | 79 (42%) | 105 (56%)
Death, n (%) | 10 (5%) | 8 (4%)
Median PFS in months (95% CI) | 16.6 (12.6, 27.2) | 8.1 (5.8, 11.1)
Hazard ratio (95% CI)a | 0.55 (0.42, 0.73)
P-valueb | < 0.0001
Overall Response Rate
Overall response rate, % (95% CI)c | 73 (66, 79) | 27 (21, 34)
Complete response, % | 1 | 0
Partial response, % | 72 | 27
Duration of Response
Number of responders | n = 137 | n = 50
Median in months (95% CI) | 23.9 (16.6, NE) | 11.1 (7.8, 16.4)
Abbreviations: BIRC, Blinded Independent Review Committee; CI, confidence interval; NE, not estimable.
aCox proportional hazards model stratified by brain metastases (absence vs. presence), WHO performance status (0 vs. ≥ 1), and prior adjuvant chemotherapy (absence vs. presence).
bLog-rank test stratified by brain metastases (absence vs. presence), WHO performance status (0 vs. ≥ 1), and prior adjuvant chemotherapy (absence vs. presence).
cClopper and Pearson exact binomial 95% CI.

There was no significant difference in OS in a pre-specified interim analysis conducted at 42% of the events required for the final analysis.

Figure 1: Kaplan-Meier Plot of Progression-Free Survival as Assessed by BIRC by Treatment Arm in ASCEND-4

Antitumor activity of ZYKADIA in the brain was assessed in patients with measurable disease as determined by the BIRC neuro-radiologist at baseline (N = 55) according to RECIST 1.1.

Table 8: BIRC Assessed CNS Responses in Patients With Measurable CNS Lesions in ASCEND-4
Intracranial Tumor Response Assessment | ZYKADIA (N = 28) | Chemotherapy (N = 27)
Overall intracranial response rate, % (95% CI)a | 57% (37, 76) | 22% (9, 42)
Complete response, % | 7% | 7%
Partial response, % | 50% | 15%
Duration of Intracranial Response
Number of responders | n = 16 | n = 6
Median in months (95% CI) | 16.6 (8.1, NE) | NE (1.5, NE)
Abbreviations: BIRC, Blinded Independent Review Committee; CI, confidence interval; CNS, central nervous system; NE, not estimable.
aClopper and Pearson exact binomial 95% CI.

Exploratory analyses of patient-reported outcome measures suggested a delay in time to development of or worsening of shortness of breath in patients treated with ZYKADIA as compared to chemotherapy. The patient-reported delay in onset or worsening of shortness of breath may be an overestimation, because patients were not blinded to treatment assignment.

14.2 Previously Treated ALK-Positive Metastatic NSCLC

The efficacy of ZYKADIA was evaluated in a multicenter, single-arm, open-label clinical trial (ASCEND-1, NCT01283516). A total of 163 patients with metastatic ALK-positive NSCLC who progressed while receiving or were intolerant to crizotinib were enrolled. The major efficacy outcome measure was objective response rate (ORR) according to RECIST v1.0 as evaluated by both investigators and BIRC. Duration of response was an additional outcome measure. All patients received ZYKADIA at a dose of 750 mg once daily under fasted conditions.

The study population characteristics were: median age 52 years, age less than 65 (87%), female (54%), White (66%), Asian (29%), never or former smoker (97%), ECOG PS 0 or 1 (87%), progression on previous crizotinib (91%), number of prior therapies 2 or more (84%), and adenocarcinoma histology (93%). Sites of extra-thoracic metastases included brain (60%), liver (42%), and bone (42%). ALK-positivity was verified retrospectively by review of local test results for 99% of patients.

Efficacy results from ASCEND-1 are summarized in Table 9.

Table 9: Overall Response Rate and Duration of Response^1 in ASCEND-1
Efficacy Parameter | Investigator Assessment (N = 163) | BIRC Assessment (N = 163)
Overall response rate, % (95% CI) | 55% (47, 62) | 44% (36, 52)
Complete response, % | 1.2% | 2.5%
Partial response, % | 53% | 41%
Duration of response, median (months) (95% CI) | 7.4 (5.4, 10.1) | 7.1 (5.6, NE)
Abbreviations: BIRC, Blinded Independent Review Committee; CI, confidence interval; NE, not estimable.
^1Overall response rate and duration of response determined by RECIST v1.0.

The analysis by the BIRC assessment was similar to the analysis by the investigator assessment.

16 HOW SUPPLIED/STORAGE AND HANDLING

ZYKADIA 150 mg capsules

Hard gelatin capsule with opaque blue cap and opaque white body; opaque blue cap marked in black ink with “LDK 150MG”, opaque white body marked in black ink with “NVR”. Available in:

Bottles of 70 capsules…………………………………………………………………………………….NDC 0078-0640-70

Store at 20°C to 25°C (68°F to 77°F); excursions permitted between 15°C to 30°C (59°F to 86°F) [see USP Controlled Room Temperature].

ZYKADIA 150 mg tablets

Film-coated tablet, light blue, round, biconvex with beveled edges, without score, debossed with “NVR” on one side and “ZY1” on the other side. Available in:

Bottles of 84 tablets…………………………………………………………………………………NDC 0078-0694-84

Store at 20°C to 25°C (68°F to 77°F); excursions permitted between 15°C to 30°C (59°F to 86°F) [see USP Controlled Room Temperature].

17 PATIENT COUNSELING INFORMATION

Advise the patient to read the FDA-approved patient labeling (Patient Information).

Gastrointestinal Adverse Reactions

Inform patients that diarrhea, nausea, vomiting, and abdominal pain are the most commonly reported gastrointestinal adverse reactions. Inform patients of supportive care options, such as antiemetic and anti-diarrheal medications. Advise patients to contact their healthcare provider for severe or intolerable gastrointestinal symptoms. Inform patients that if vomiting occurs during the course of treatment, they should not take an additional dose, but should continue with the next scheduled dose of ZYKADIA [see Warnings and Precautions (5.1)].

Hepatotoxicity

Inform patients of the signs and symptoms of hepatotoxicity. Advise patients to contact their healthcare provider immediately for signs or symptoms of hepatotoxicity [see Warnings and Precautions (5.2)].

Interstitial Lung Disease/Pneumonitis

Inform patients of the risks of severe or fatal ILD/pneumonitis. Advise patients to contact their healthcare provider immediately to report new or worsening respiratory symptoms [see Warnings and Precautions (5.3)].

Arrhythmias

Inform patients of the risks of QTc interval prolongation and bradycardia. Advise patients to contact their healthcare provider immediately to report new chest pain or discomfort, changes in heartbeat, palpitations, dizziness, lightheadedness, fainting, and changes in or new use of heart or blood pressure medications [see Warnings and Precautions (5.4, 5.6)].

Hyperglycemia

Inform patients of the signs and symptoms of hyperglycemia. Advise patients to contact their healthcare provider immediately for signs or symptoms of hyperglycemia [see Warnings and Precautions (5.5)].

Pancreatitis

Inform patients of the signs and symptoms of pancreatitis and the need to monitor lipase and amylase levels prior to the start of treatment and periodically thereafter as clinically indicated [see Warnings and Precautions (5.7)].

Photosensitivity

Inform patients of the signs and symptoms of photosensitivity. Advise patients to avoid prolonged sun exposure and to use sunscreen or protective clothing during treatment with ZYKADIA [see Adverse Reactions (6.1)].

Embryo-Fetal Toxicity

- Advise pregnant women and females of reproductive potential of the potential risk to a fetus and to inform their healthcare provider of a known or suspected pregnancy [see Warnings and Precautions (5.8), Use in Specific Populations (8.3)].
- Advise females of reproductive potential to use effective contraception during treatment with ZYKADIA and for 6 months following completion of therapy [see Use in Specific Populations (8.3)].
- Advise males with female partners of reproductive potential to use condoms during treatment with ZYKADIA and for 3 months following completion of therapy [see Use in Specific Populations (8.3), Nonclinical Toxicology (13.1)].

Lactation

Advise women not to breastfeed during treatment with ZYKADIA and for 2 weeks following completion of therapy [see Use in Specific Populations (8.2)].

Drug Interactions

Inform patients not to consume grapefruit and grapefruit juice during treatment with ZYKADIA [see Drug Interactions (7.1)].

Dosing Instructions

Advise patients to take ZYKADIA with food [see Dosage and Administration (2.2)]. Advise patients to make up a missed dose of ZYKADIA unless the next dose is due within 12 hours [see Dosage and Administration (2.2)].

Distributed by:
Novartis Pharmaceuticals Corporation
East Hanover, New Jersey 07936

© Novartis

T2021-132

PATIENT INFORMATION
ZYKADIA® (zye kaye' dee ah)
(ceritinib) capsules
(ceritinib) tablets

Read this Patient Information leaflet that comes with ZYKADIA before you start taking it and each time you get a refill. There may be new information. This information does not take the place of talking to your healthcare provider about your medical condition or treatment.

What is the most important information I should know about ZYKADIA?
ZYKADIA may cause serious side effects, including:
Stomach and intestinal (gastrointestinal) problems. ZYKADIA may cause stomach and intestinal problems, including diarrhea, nausea, vomiting, and stomach-area pain. Follow your healthcare provider’s instructions about taking medicines to help with these symptoms. Call your healthcare provider for advice if your symptoms are severe or cannot be tolerated.
Liver problems. ZYKADIA may cause liver injury. Your healthcare provider should do blood tests at least every month to check your liver during treatment with ZYKADIA. Tell your healthcare provider right away if you get any of the following:

• you feel tired

• you have itchy skin

• your skin or the whites of your eyes turn yellow

• you have nausea or vomiting

• you have a decreased appetite

• you have pain on the right side of your stomach-area

• your urine turns dark or brown (tea color)

• you bleed or bruise more easily than normal

Lung problems (pneumonitis). ZYKADIA may cause severe or life-threatening inflammation of the lungs during treatment that can lead to death. Symptoms may be similar to those symptoms from lung cancer. Tell your healthcare provider right away if you have any new or worsening symptoms, including:

• trouble breathing or shortness of breath

• cough with or without mucus

• fever

• chest pain

Heart problems. ZYKADIA may cause very slow, very fast, or abnormal heartbeats. Your healthcare provider may check your heart during treatment with ZYKADIA. Tell your healthcare provider right away if you feel new chest pain or discomfort, dizziness or lightheadedness, if you faint, or have abnormal heartbeats. Tell your healthcare provider if you start to take or have any changes in heart or blood pressure medicines.
See "What are the possible side effects of ZYKADIA?" for more information about side effects.

What is ZYKADIA?
ZYKADIA is a prescription medicine that is used to treat people with non-small cell lung cancer (NSCLC) that:

- is caused by a defect in a gene called anaplastic lymphoma kinase (ALK), and
- has spread to other parts of the body

It is not known if ZYKADIA is safe and effective in children.

Before you take ZYKADIA, tell your healthcare provider about all of your medical conditions, including if you:

- have liver problems
- have diabetes or high blood sugar
- have heart problems, including a condition called long QT syndrome
- have or have had pancreatitis
- are pregnant or plan to become pregnant. ZYKADIA can harm your unborn baby. Females who are able to become pregnant should use an effective method of birth control during treatment with ZYKADIA and for 6 months after stopping ZYKADIA. Talk to your healthcare provider about birth control methods that may be right for you. Tell your healthcare provider right away if you become pregnant or think that you may be pregnant.
  - Males with female partners who are able to become pregnant should use condoms during treatment with ZYKADIA and for 3 months after stopping ZYKADIA.
- are breastfeeding or plan to breastfeed. It is not known if ZYKADIA passes into your breast milk. Do not breastfeed during treatment with ZYKADIA and for 2 weeks after stopping ZYKADIA.

Tell your healthcare provider about all the medicines you take, including prescription medicines, over-the-counter medicines, vitamins, and herbal supplements.

How should I take ZYKADIA?

- Take ZYKADIA exactly as your healthcare provider tells you. Do not change your dose or stop taking ZYKADIA unless your healthcare provider tells you to.
- Take ZYKADIA one time a day.
- Take ZYKADIA with food.
- If you vomit after taking ZYKADIA, do not take an additional dose. Continue with the next scheduled dose.
- If you miss a dose of ZYKADIA, take it as soon as you remember. If your next dose is due within 12 hours, then skip the missed dose. Just take the next dose at your regular time.

What should I avoid while taking ZYKADIA?

- You should not drink grapefruit juice or eat grapefruit during treatment with ZYKADIA. It may make the amount of ZYKADIA in your blood increase to a harmful level.
- Avoid spending time in sunlight during treatment with ZYKADIA. Your skin may become more sensitive to the sun and you may burn more easily. Use sunscreen and wear protective clothing that covers your skin to help protect against sunburn.

What are the possible side effects of ZYKADIA?
ZYKADIA may cause serious side effects, including:

- See "What is the most important information I should know about ZYKADIA?"
- High blood sugar (hyperglycemia). People who have diabetes or glucose intolerance or who take a corticosteroid medicine have an increased risk of high blood sugar with ZYKADIA. Your healthcare provider will check your blood sugar level before starting ZYKADIA and as needed during treatment with ZYKADIA. Call your healthcare provider right away if you have any symptoms of high blood sugar, including:

• increased thirst

• increased hunger

• headaches

• trouble thinking or concentrating

• urinating often

• blurred vision

• tiredness

• your breath smells like fruit

- Inflammation of the pancreas (pancreatitis). ZYKADIA can cause pancreatitis that has led to death. You may develop increased pancreatic enzyme blood levels, which may be a sign of pancreatitis. Signs and symptoms of pancreatitis include upper abdominal pain that may spread to the back and get worse with eating. Your healthcare provider should do blood tests to check your pancreatic enzyme blood levels before you start ZYKADIA and as needed during your treatment.

The most common side effects of ZYKADIA include:

- stomach and intestinal (gastrointestinal) problems. See “What is the most important information I should know about ZYKADIA?”
- tiredness, decreased appetite, and weight loss

These are not all of the possible side effects of ZYKADIA. For more information, ask your healthcare provider or pharmacist. Call your doctor for medical advice about side effects. You may report side effects to FDA at 1-800-FDA-1088.

How should I store ZYKADIA?

- Store ZYKADIA at room temperature between 68°F to 77°F (20°C to 25°C).

Keep ZYKADIA and all medicines out of the reach of children.

General information about the safe and effective use of ZYKADIA
Medicines are sometimes prescribed for purposes other than those listed in a Patient Information leaflet. Do not use ZYKADIA for a condition for which it was not prescribed. Do not give it to other people, even if they have the same symptoms you have. It may harm them. You can ask your healthcare provider or pharmacist for more information about ZYKADIA that is written for health professionals.

What are the ingredients in ZYKADIA?
Active ingredient: ceritinib
Inactive ingredients capsules: colloidal silicon dioxide, hard gelatin capsule shells, low-substituted hydroxypropyl cellulose, magnesium stearate, microcrystalline cellulose, and sodium starch glycolate. Capsule shell contains FD&C Blue # 2, gelatin, and titanium dioxide.
Inactive ingredients tablets: Tablet core: colloidal silicon dioxide, croscarmellose sodium, low-substituted hydroxypropyl cellulose, magnesium stearate, microcrystalline cellulose and povidone. Tablet coating: FD&C Blue # 2 aluminum lake, hypromellose, polyethylene glycol 4000, talc, and titanium dioxide.
Distributed by: Novartis Pharmaceuticals Corporation, East Hanover, New Jersey 07936. For more information, go to www.zykadia.com or call 1-888-669-6682.

This Patient Information has been approved by the U.S. Food and Drug Administration.

Revised: January 2025

T2025-01

PRINCIPAL DISPLAY PANEL

NDC 0078-0694-84

Zykadia®

(ceritinib) tablets

150 mg

84 Tablets

Rx only

NOVARTIS